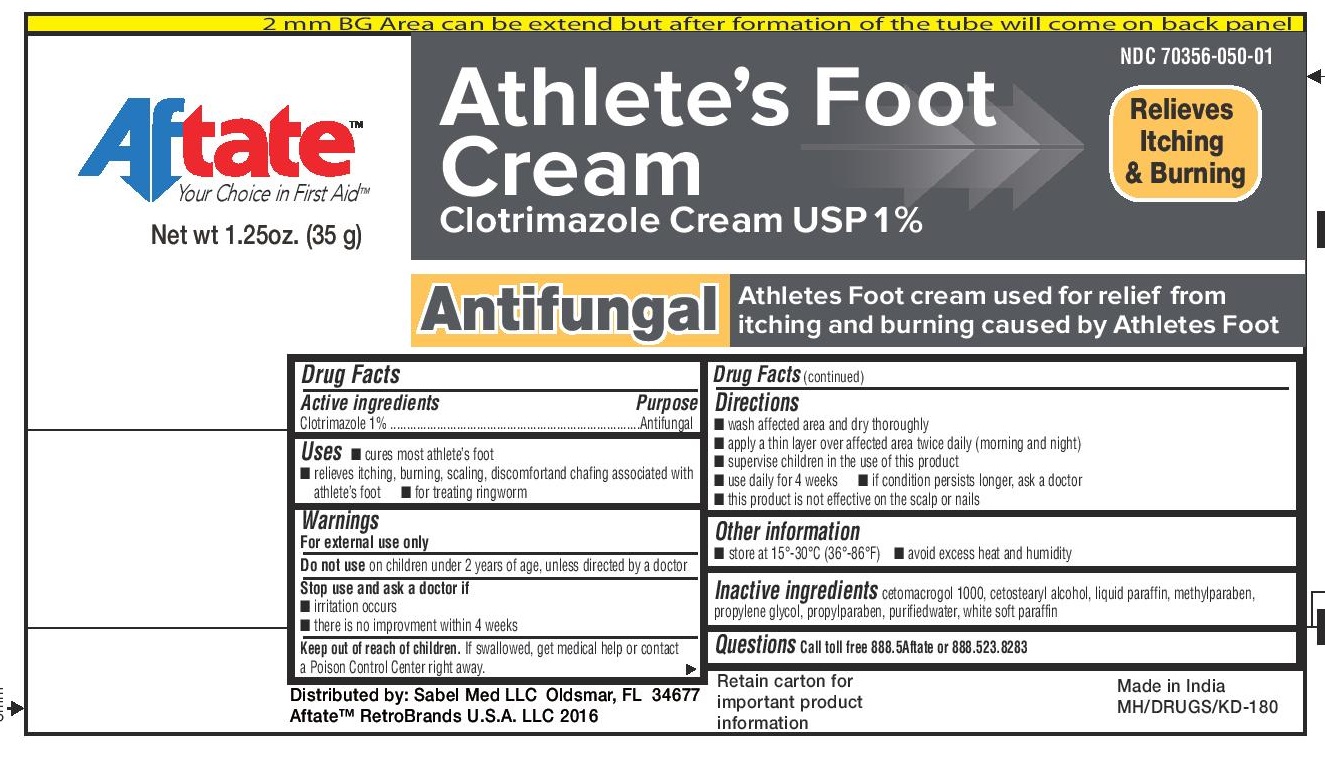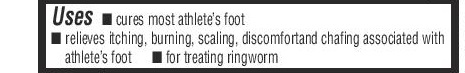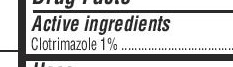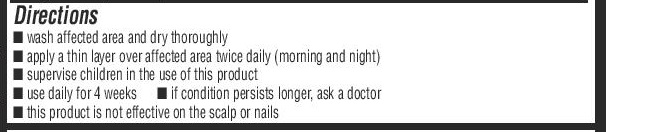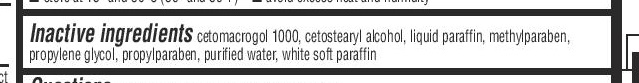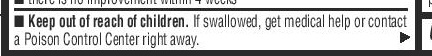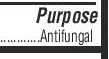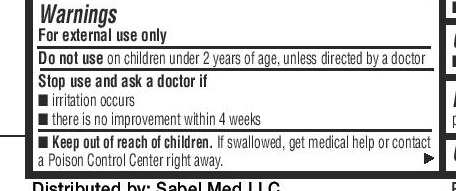 DRUG LABEL: Athlete Foot Cream with Clotrimazole
NDC: 70356-050 | Form: CREAM
Manufacturer: Sabel Med LLC
Category: otc | Type: HUMAN OTC DRUG LABEL
Date: 20160414

ACTIVE INGREDIENTS: CLOTRIMAZOLE 1 g/100 g
INACTIVE INGREDIENTS: PROPYLPARABEN; WATER; PARAFFIN; CETETH-20; CETOSTEARYL ALCOHOL; MINERAL OIL; METHYLPARABEN; PROPYLENE GLYCOL

Athlete's Foot Cream with1% Clotrimazole